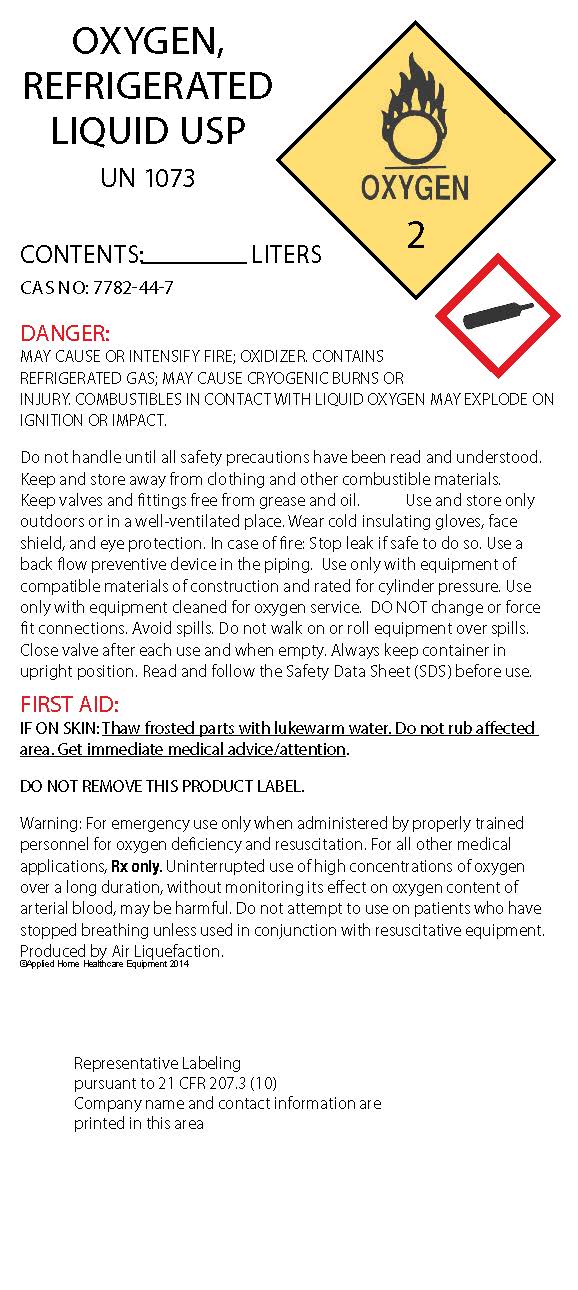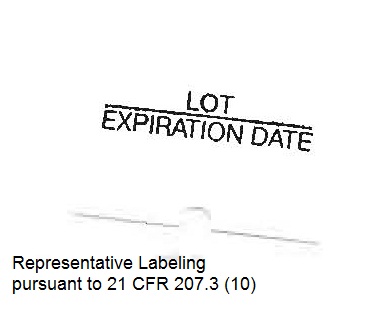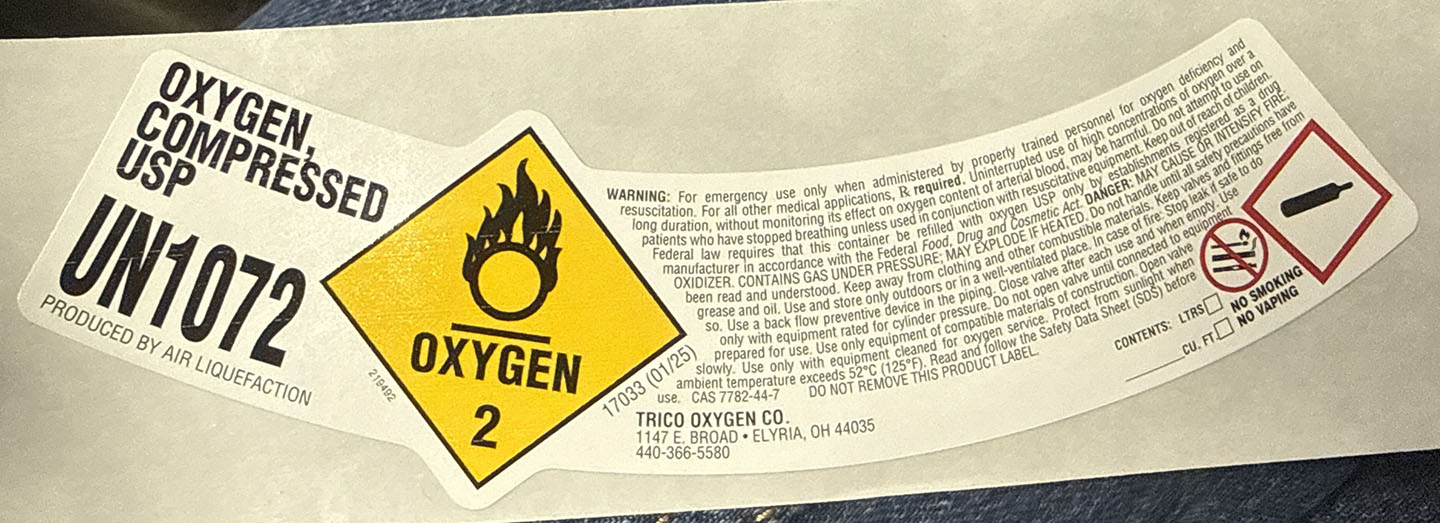 DRUG LABEL: Oxygen
NDC: 43713-001 | Form: GAS
Manufacturer: Trico Oxygen
Category: prescription | Type: HUMAN PRESCRIPTION DRUG LABEL
Date: 20251215

ACTIVE INGREDIENTS: OXYGEN 99 L/100 L

Oxygen, USP

Principal for Oxygen Product

OXYGEN, COMPRESSED

USP

UN1072

PRODUCED BY AIR LIQUEFACTION

OXYGEN 2

(Flame over circle symbol)

WARNING: For emergency use only when administered by properly trained personnel and resuscitation. For all other medical applications, it is required to use oxygen of limited duration, without monitoring its effect on oxygen content of arterial blood. Uninterrupted use on patients who have stopped breathing unless equipped with a resuscitator may be hazardous. Federal law mandates that this container be refilled only by the manufacturer or distributor of compressed gases. Food, Drug and Cosmetic Act.

OXIDIZER. CONTAINS GAS UNDER PRESSURE. May explode if heated. Keep away from heat, sparks, open flames and grease and oil. Use and store with adequate ventilation. Use a slow leak preventive device in the pressure control outlet. Use only with equipment rated for cylinder pressure. Do not oil or grease cylinder or fittings. Do not remove or deface this label. Protect from physical damage. Use only with proper instructions. Keep cylinder secured at all times. Use equipment cleaned for oxygen service. Protect from contamination. Store and use in a well-ventilated place.

Ambient temperature exceeds 52°C (125°F). Read and follow the Safety Data Sheet (SDS) before use.

CAS 7782-44-7

DO NOT REMOVE THIS PRODUCT LABEL

TRICO OXYGEN CO.

1117 E. BROAD – ELYRIA, OH 44035

440-366-5580

CONTENTS: ___ LTRS

CU. FT. ___

NO SMOKING

NO VAPING

OXYGEN,

REFRIGERATED

LIQUID USP

UN 1073

CONTENTS ________________LITERS

CAS NO: 7782-44-7

DANGER:

MAY CAUSE OR INTENSIFY FIRE; OXIDIZER. CONTAINS

REFRIGERATED GAS; MAY CAUSE CRYOGENIC BURNS OR

INJURY. COMBUSTIBLES IN CONTACT WITH LIQUID OXYGEN MAY EXPLODE ON

IGNITION OR IMPACT.

Do not handle until all safety precautions have been read and understood.

Keep and store away from clothing and other combustible materials.

Keep valves and fittings free from grease and oil. Use and store only

outdoors or in a well-ventilated place. Wear cold insulating gloves, face

shield, and eye protection. In case of fire: Stop leak if safe to do so. Use a

back flow preventive device in the piping. Use only with equipment of

compatible materials of construction and rated for cylinder pressure. Use

only with equipment cleaned for oxygen service. DO NOT change or force

fit connections. Avoid spills. Do not walk on or roll equipment over spills.

Close valve after each use and when empty. Always keep container in

upright position. Read and follow the Safety Data Sheet (SDS) before use.

FIRST AID:

IF ON SKIN: Thaw frosted parts with lukewarm water. Do not rub affected

area. Get immediate medical advice/attention.

DO NOT REMOVE THIS PRODUCT LABEL.

Warning: For emergency use only when administered by properly trained

personnel for oxygen deficiency and resuscitation. For all other medical

applications, Rx only. Uninterrupted use of high concentrations of oxygen

over a long duration, without monitoring its effect on oxygen content of

arterial blood, may be harmful. Do not attempt to use on patients who have

stopped breathing unless used in conjunction with resuscitative equipment.

Produced by Air Liquefaction.